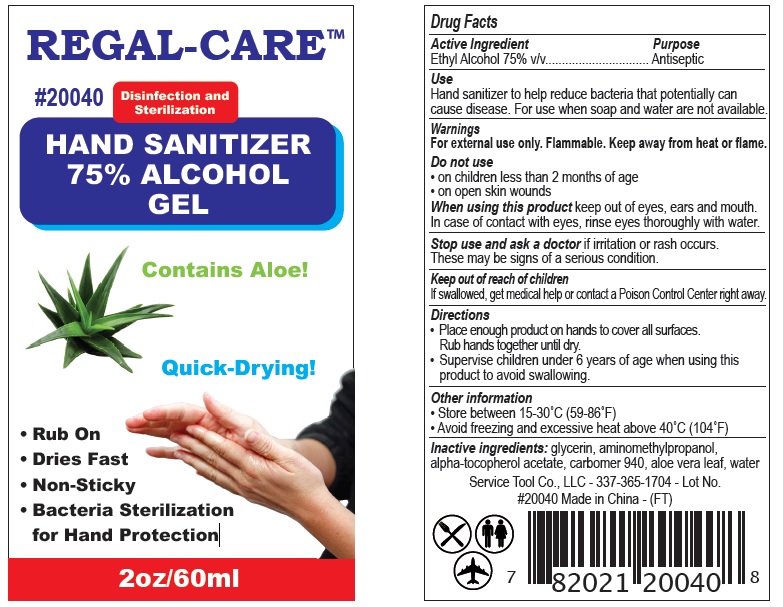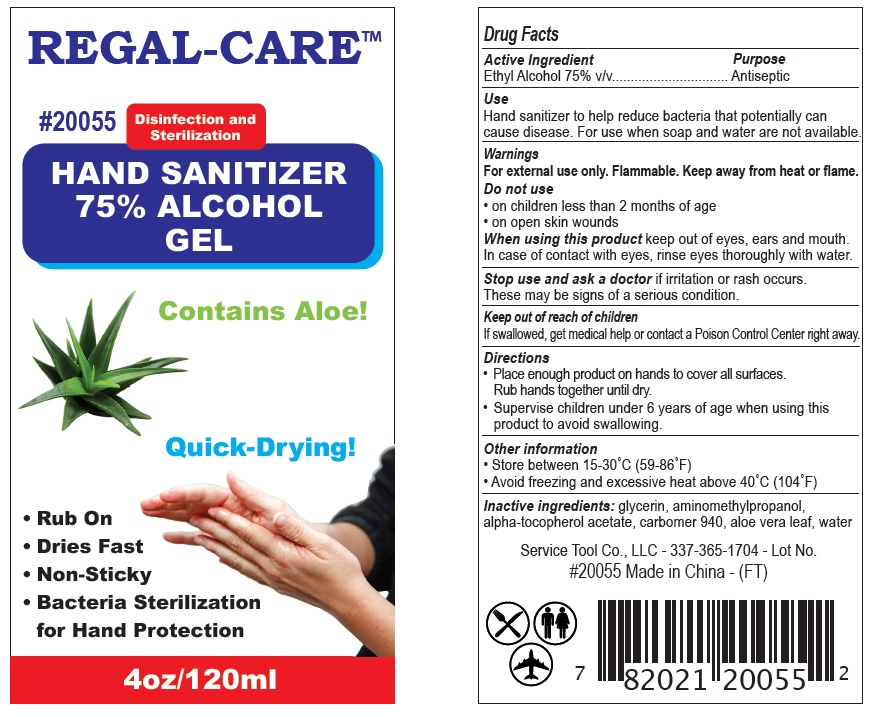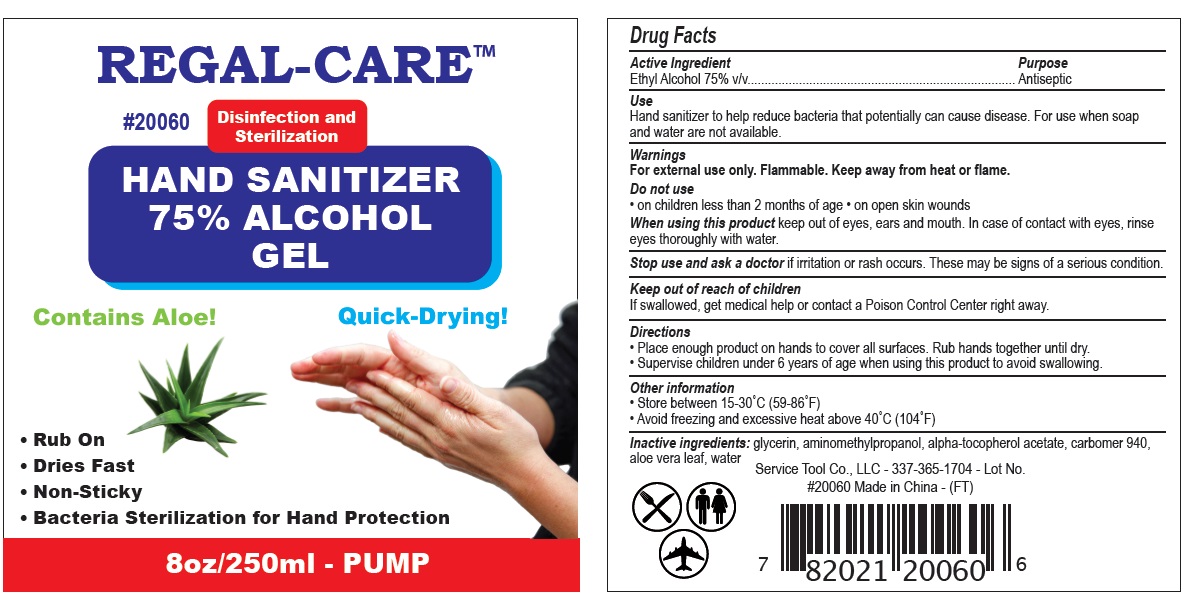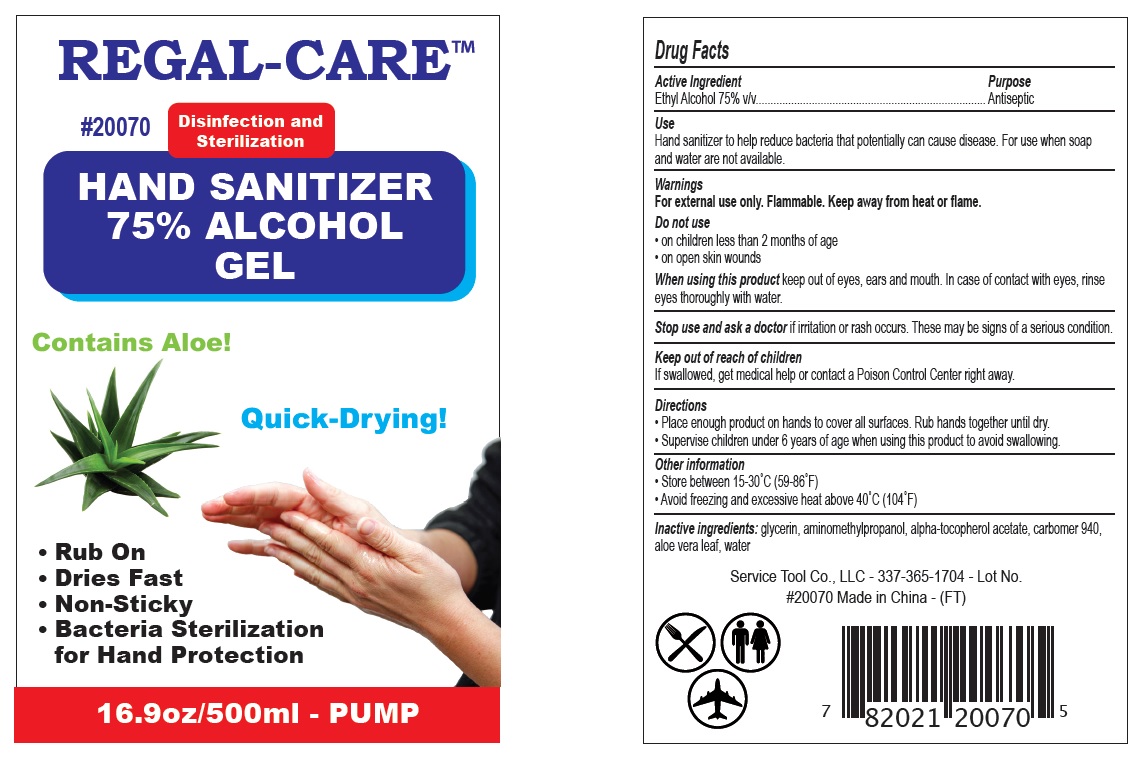 DRUG LABEL: REGAL CARE
NDC: 78710-075 | Form: GEL
Manufacturer: SERVICE TOOL COMPANY, L.L.C.
Category: otc | Type: HUMAN OTC DRUG LABEL
Date: 20200604

ACTIVE INGREDIENTS: ALCOHOL 75 mL/100 mL
INACTIVE INGREDIENTS: GLYCERIN; AMINOMETHYLPROPANOL; .ALPHA.-TOCOPHEROL ACETATE; CARBOMER 940; ALOE VERA LEAF; WATER

Active Ingredient

Ethyl Alcohol 75% v/v

Purpose

Antiseptic

Use

Hand Sanitizer to help reduce bacteria that potentially can cause disease. For use when soap and water are not available.

Warnings

For external use only. Flammable. Keep away from heat or flame

Do not use

- on children less than 2 months of age
- on open skin wounds

When using this product

keep out of eyes, ears, and mouth. In case of contact with eyes, rinse eyes thoroughly with water.

Stop use and ask a doctor

if irritation or rash occurs. These may be signs of a serious condition.

Keep out of reach of children.

If swallowed, get medical help or contact a Poison Control Center right away.

Directions

- Place enough product on hands to cover all surfaces. Rub hands together until dry.
- Supervise children under 6 years of age when using this product to avoid swallowing.

Other information

- Store between 15-30C (59-86F)
- Avoid freezing and excessive heat above 40C (104F)

Inactive ingredients

glycerin, aminomethylpropanol, alpha-tocopherol acetate, carbomer 940, aloe vera leaf, water

Package Label - Principal Display Panel

NDC 78710-075-02

REGAL-CARETM

# 20040

Disinfection and Sterilization

HAND SANITIZER 75% ALCOHOL GEL

Contains Aloe!

Quick-Drying!

- Rub On
- Dries Fast
- Non-Sticky
- Bacteria Sterilization for Hand Protection

2 oz/ 60 mL

78710-075-04

REGAL-CARETM

# 20055

Disinfection and Sterilization

HAND SANITIZER 75% ALCOHOL GEL

Contains Aloe!

Quick-Drying!

- Rub On
- Dries Fast
- Non-Sticky
- Bacteria Sterilization for Hand Protection

4 oz/ 120 mL

78710-075-08

REGAL-CARETM

# 20060

Disinfection and Sterilization

HAND SANITIZER 75% ALCOHOL GEL

Contains Aloe!

Quick-Drying!

- Rub On
- Dries Fast
- Non-Sticky
- Bacteria Sterilization for Hand Protection

8 oz/ 250 mL - PUMP

78710-075-17

REGAL-CARETM

# 20070

Disinfection and Sterilization

HAND SANITIZER 75% ALCOHOL GEL

Contains Aloe!

Quick-Drying!

- Rub On
- Dries Fast
- Non-Sticky
- Bacteria Sterilization for Hand Protection

16.9 oz/ 500 mL - PUMP